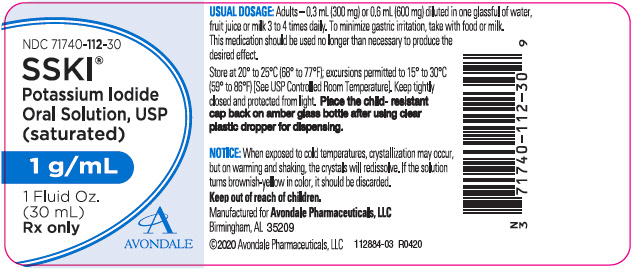 DRUG LABEL: SSKI
NDC: 71740-112 | Form: SOLUTION
Manufacturer: Avondale Pharmaceuticals, LLC
Category: prescription | Type: HUMAN PRESCRIPTION DRUG LABEL
Date: 20250709

ACTIVE INGREDIENTS: Potassium Iodide 1 g/1 mL
INACTIVE INGREDIENTS: sodium thiosulfate

SSKI®
Potassium Iodide Oral Solution, USP (Saturated)
1 g/mL

Rx only

Description

SSKI® (potassium iodide oral solution, USP) is a saturated solution of potassium iodide containing 1 gram of potassium iodide per mL.

Clinical Pharmacology

Potassium iodide is thought to act as an expectorant by increasing respiratory tract secretions and thereby decreasing the viscosity of mucus.

Indications and Usage

SSKI® (potassium iodide oral solution, USP) is for use as an expectorant in the symptomatic treatment of chronic pulmonary diseases where tenacious mucus complicates the problem, including bronchial asthma, bronchitis and pulmonary emphysema.

Contraindications

Contraindicated in patients with a known sensitivity to iodides.

Warnings

Potassium iodide can cause fetal harm, abnormal thyroid function, and goiter when administered to a pregnant woman. Because of the possible development of fetal goiter, if the drug is used during pregnancy or if the patient becomes pregnant during therapy, apprise the patient of the potential hazard.

Precautions

General

In some patients, prolonged use of iodides can lead to hypothyroidism. Iodides should be used with caution in patients having Addison's disease, cardiac disease, hyperthyroidism, myotonia congenita, tuberculosis, acute bronchitis, or renal function impairment.

Drug Interactions

Concurrent use with lithium or antithyroid drugs may potentiate the hypothyroid and goitrogenic effects of these medications. Concurrent use with potassium-containing medications, potassium-sparing diuretics and angiotensin-converting enzyme inhibitors (ACE inhibitors) may result in hyperkalemia and cardiac arrhythmias or cardiac arrest.

Drug/Laboratory Test Interactions

Thyroid function tests may be altered by iodide.

Pregnancy

see "Warnings" section.

Nursing Mothers

Potassium iodide is excreted in breast milk. Use by nursing mothers may cause skin rash and thyroid suppression in the infant.

Pediatric Use

Safety and effectiveness in children have not been established.

Adverse Reactions

The most frequent adverse reactions to potassium iodide are stomach upset, diarrhea, nausea, vomiting, stomach pain, skin rash, and salivary gland swelling or tenderness. Less frequent adverse reactions include gastrointestinal bleeding, confusion, irregular heartbeat, numbness, tingling, pain or weakness in hands or feet, unusual tiredness, weakness or heaviness of legs, fever, and swelling of neck or throat. Thyroid adenoma, goiter, and myxedema are possible side effects.

Iodism or chronic iodine poisoning may occur during prolonged treatment or with the use of high doses. The symptoms of iodism include burning of mouth or throat, severe headache, metallic taste, soreness of teeth and gums, symptoms of head cold, irritation of the eyes with swelling of the eyelids, unusual increase in salivation, acneform skin lesions in the seborrheic areas, and rarely, severe skin eruptions. If symptoms of iodism appear, the drug should be withdrawn and the patient given appropriate supportive therapy.

Hypersensitivity to iodides may occur and may be manifested by angioedema, cutaneous and mucosal hemorrhage, and signs and symptoms resembling serum sickness, such as fever, arthralgia, lymph node enlargement, and eosinophilia.

Overdosage

Acute toxicity from potassium iodide is relatively rare. An occasional individual may show marked sensitivity and the onset of acute poisoning can occur immediately or hours after administration. Angioedema, laryngeal edema and cutaneous hemorrhages may occur.

Iodism or chronic iodine poisoning may occur during prolonged treatment or with the use of high doses. Symptoms of iodism typically disappear soon after discontinuation of the drug. Abundant fluid and salt intake aids in iodide elimination.

Dosage and Administration

Adults

0.3 ml (300 mg) or 0.6 ml (600 mg) diluted in one glassful of water, fruit juice or milk 3 to 4 times daily. To minimize gastric irritation, take with food or milk.

This medication should be used no longer than necessary to produce the desired effect.

How Supplied

SSKI® (potassium iodide oral solution, USP) is supplied in 1 fluid ounce (30 ml) bottles (NDC 71740-112-30) with a calibrated dropper marked to deliver 0.3 ml (300 mg) and 0.6 ml (600 mg); and 8 fluid ounce (237 ml) bottles (NDC 71740-112-08). Inactive ingredient: Sodium thiosulfate as a preservative.

STORAGE AND HANDLING

Store at 20° to 25°C (68° to 77°F); excursions permitted to 15° to 30°C (59° to 86°F) [See USP Controlled Room Temperature]. Keep tightly closed and protected from light.

For the 237mL bottle, dispense in tight, light-resistant containers with child-resistant closures. For the 30mL bottle, place the child-resistant cap back on the amber glass bottle after using the clear plastic dropper for dispensing.

Notice: When exposed to cold temperatures, crystallization may occur, but on warming and shaking, the crystals will redissolve. If the solution turns brownish-yellow in color, it should be discarded.

Manufactured for
Avondale Pharmaceuticals, LLC
Birmingham, AL 35209

112886-02

Revised 0420

© 2020 Avondale Pharmaceuticals, LLC

PRINCIPAL DISPLAY PANEL - 30 mL Bottle Label

NDC 71740-112-30

SSKI®

Potassium Iodide
Oral Solution, USP
(saturated)

1 g/mL

1 Fluid Oz.
(30 mL)
Rx only

AVONDALE